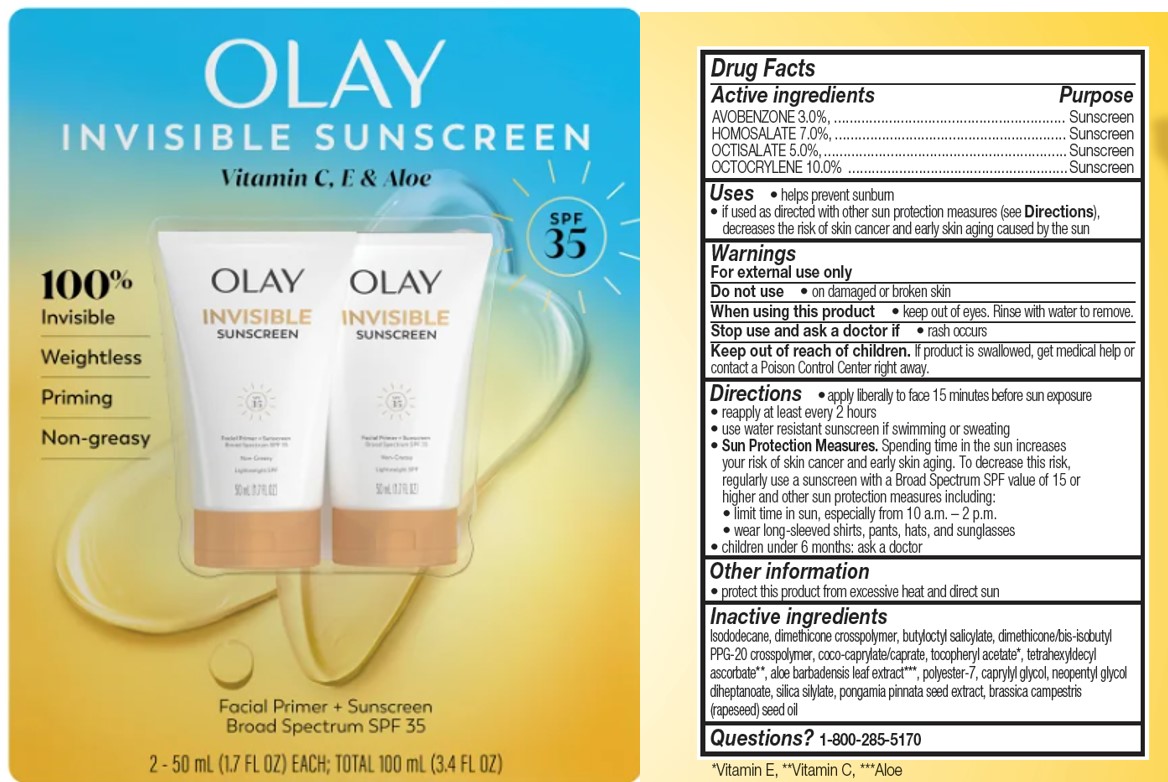 DRUG LABEL: Olay Invisible Sunscreen Facial Primer plus Sunscreen Broad Spectrum SPF 35
NDC: 84126-161 | Form: LOTION
Manufacturer: The Procter & Gamble Manufacturing Company
Category: otc | Type: HUMAN OTC DRUG LABEL
Date: 20250815

ACTIVE INGREDIENTS: AVOBENZONE 3 g/100 mL; HOMOSALATE 7 g/100 mL; OCTISALATE 5 g/100 mL; OCTOCRYLENE 10 g/100 mL
INACTIVE INGREDIENTS: ISODODECANE; PONGAMIA PINNATA SEED; POLYESTER-7; ALOE BARBADENSIS LEAF; DIMETHICONE/BIS-ISOBUTYL PPG-20 CROSSPOLYMER; SILICA DIMETHYL SILYLATE; CAPRYLYL GLYCOL; .ALPHA.-TOCOPHEROL ACETATE; BUTYLOCTYL SALICYLATE; COCO-CAPRYLATE/CAPRATE; TETRAHEXYLDECYL ASCORBATE; BRASSICA CAMPESTRIS (RAPESEED) SEED OIL; DIMETHICONE CROSSPOLYMER; NEOPENTYL GLYCOL DIHEPTANOATE

Olay Invisible Sunscreen Facial Primer plus Sunscreen Broad Spectrum SPF 35

Drug Facts

ACTIVE INGREDIENT

Avobenzone 3.0%

Homosalate 7.0%

Octisalate 5.0%

Octocrylene 10.0%

PURPOSE

Sunscreen

Uses

- helps prevent sunburn
- if used as directed with other sun protection measures (see Directions), decreases the risk of skin cancer and early skin aging caused by the sun

Warnings

For external use only

Do not use on damaged or broken skin

When using this product keep out of eyes. Rinse with water to remove.

Stop use and ask a doctor if rash occurs

Keep out of reach of children. If product is swallowed, get medical help or contact a Poison Control Center right away.

Directions

- apply liberally 15 minutes before sun exposure
- reapply at least every 2 hours
- use water resistant sunscreen if swimming or sweating
- Sun Protection Measures. Spending time in the sun increases your risk of skin cancer and early skin aging. To decrease this risk, regularly use a sunscreen with a Broad Spectrum SPF value of 15 or higher and other sun protection measures including:
  - limit time in sun, especially from 10 a.m. – 2 p.m.
  - wear long-sleeved shirts, pants, hats, and sunglasses
- children under 6 months: ask a doctor

Other information

- protect this product from excessive heat and direct sun

Inactive ingredients

Isododecane, dimethicone crosspolymer, butyloctyl salicylate, dimethicone/bis-isobutyl PPG-20 crosspolymer, coco-caprylate/caprate, tocopheryl acetate, tetrahexyldecyl ascorbate, aloe barbadensis leaf extract, polyester-7, caprylyl glycol, neopentyl glycol diheptanoate, silica silylate, pongamia pinnata seed extract, brassica campestris (rapeseed) seed oil

Questions or comments?

Call 1-800-285-5170

Dist. by PROCTER & GAMBLE,
CINCINNATI, OH 45202

PACKAGE LABEL

OLAY

INVISIBLE SUNSCREEN

VITAMIN C, E & Aloe

SPF 35

Facial Primer + Sunscreen

Broad Spectrum SPF 35

2 - 50 mL (1.7 FL OZ) EACH; TOTAL 100 mL (3.4 FL OZ)